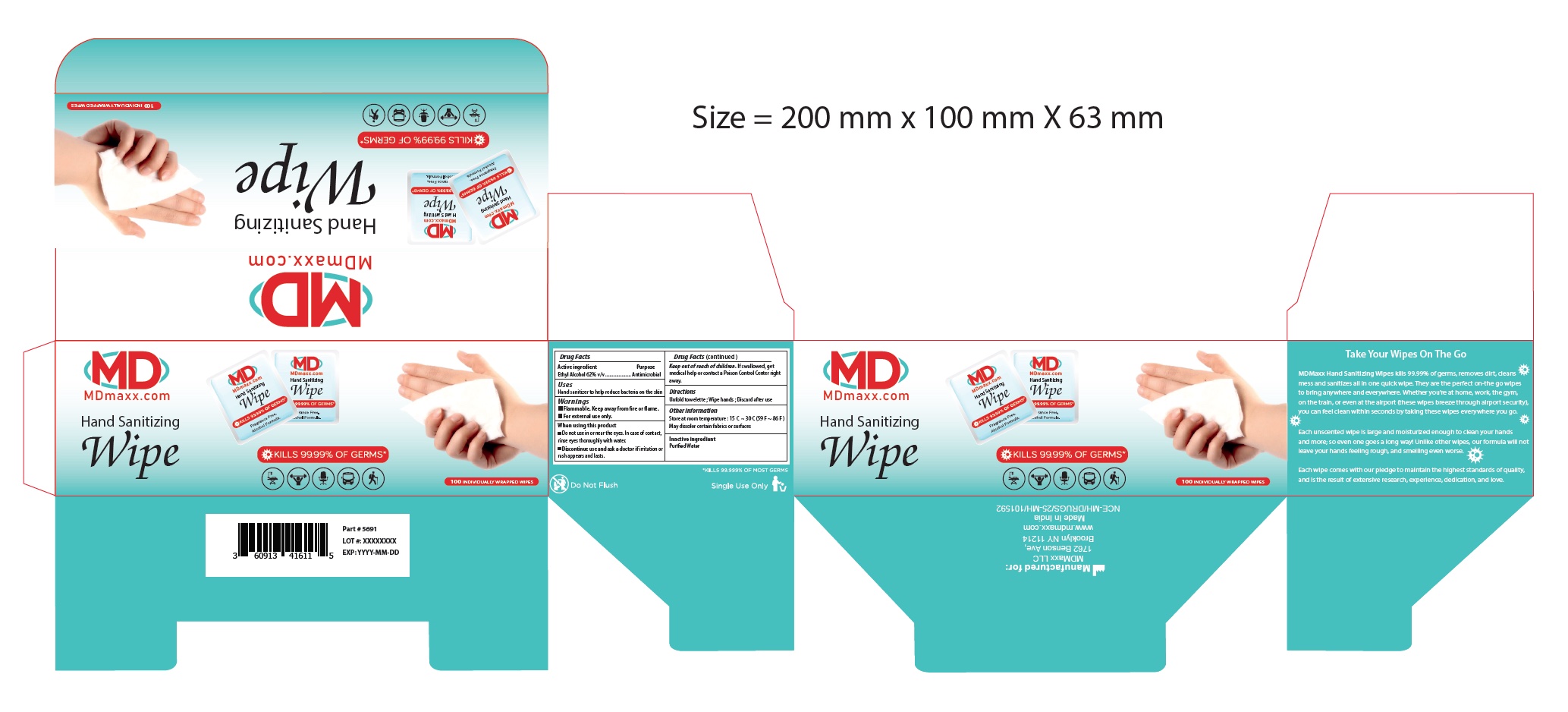 DRUG LABEL: Hand Sanitizing Wipes
NDC: 60913-416 | Form: SWAB
Manufacturer: Phoenix Healthcare Solutions LLC
Category: otc | Type: HUMAN OTC DRUG LABEL
Date: 20251023

ACTIVE INGREDIENTS: ALCOHOL 0.62 mL/1 mL
INACTIVE INGREDIENTS: WATER

MDmaxx Hand Sanitizing Wipes

Active Ingredient(s)

Ethyl Alcohol 62% v/v. Purpose: Antimicrobial

Purpose

Antimicrobial

Use

Hand Sanitizer to help reduce bacteria on the skin.

Warnings

Flammable. Keep away from fire or flame.

For external use only.

When using this product

Do not use in or near the eyes. In case of contact rinse eyes thouroughly with water.
Discontinue use and ask a doctor if irritation or rash appears and lasts.

Keep out of reach of children. If swallowed, get medical help or contact a Poison Control Center right away.

Directions

Unfold towelette; wipe hands; discard after use.

Other information

- Store between 15C -30C (59F-86F)
- May discolor certain fabrics or surfaces.

Inactive ingredients

Purified water